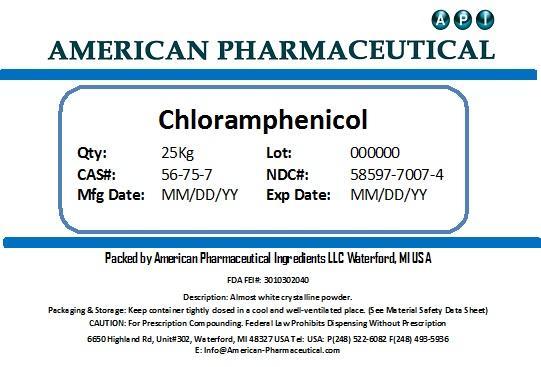 DRUG LABEL: Chloramphenicol
NDC: 58597-7007 | Form: POWDER
Manufacturer: AMERICAN PHARMACEUTICAL INGREDIENTS LLC
Category: other | Type: BULK INGREDIENT
Date: 20131101

ACTIVE INGREDIENTS: CHLORAMPHENICOL 1 g/1 g

Chloramphenicol